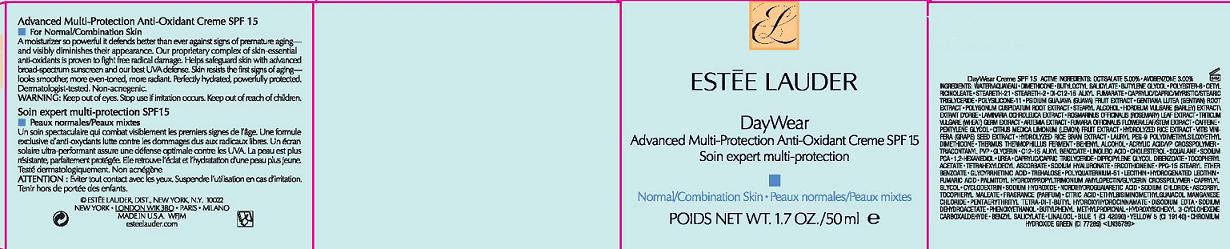 DRUG LABEL: DAYWEAR
NDC: 11559-009 | Form: CREAM
Manufacturer: ESTEE LAUDER INC
Category: otc | Type: HUMAN OTC DRUG LABEL
Date: 20110405

ACTIVE INGREDIENTS: OCTISALATE 5.0 mL/100 mL; AVOBENZONE 3.0 mL/100 mL
INACTIVE INGREDIENTS: WATER; BUTYLENE GLYCOL; DIMETHICONE; GLYCERIN; CHOLESTEROL; SQUALANE; CITRIC ACID MONOHYDRATE; LECITHIN, SOYBEAN; BUTYLATED HYDROXYTOLUENE; PHENOXYETHANOL

ACTIVE INGREDIENTS: OCTISALATE 5.00% [] AVOBENZONE 3.00%

INACTIVE INGREDIENT

INACTIVE INGREDIENTS: WATER\AQUA\EAU [] DIMETHICONE [] BUTYLOCTYL SALICYLATE [] BUTYLENE GLYCOL [] POLYESTER-8 [] CETYL RICINOLEATE [] STEARETH-21 [] STEARETH-2 [] DI-C12-15 ALKYL FUMARATE [] CAPRYLIC/CAPRIC/MYRISTIC/STEARIC TRIGLYCERIDE [] POLYSILICONE-11 [] PSIDIUM GUAJAVA (GUAVA) FRUIT EXTRACT [] GENTIANA LUTEA (GENTIAN) ROOT EXTRACT [] POLYGONUM CUSPIDATUM ROOT EXTRACT [] STEARYL ALCOHOL [] HORDEUM VULGARE (BARLEY) EXTRACT\EXTRAIT D'ORGE [] LAMINARIA OCHROLEUCA EXTRACT [] ROSMARINUS OFFICINALIS (ROSEMARY) LEAF EXTRACT [] TRITICUM VULGARE (WHEAT) GERM EXTRACT [] ARTEMIA EXTRACT [] FUMARIA OFFICINALIS FLOWER/LEAF/STEM EXTRACT [] CAFFEINE [] PENTYLENE GLYCOL [] CITRUS MEDICA LIMONUM (LEMON) FRUIT EXTRACT [] HYDROLYZED RICE EXTRACT [] VITIS VINIFERA (GRAPE) SEED EXTRACT [] HYDROLYZED RICE BRAN EXTRACT [] LAURYL PEG-9 POLYDIMETHYLSILOXYETHYL DIMETHICONE [] THERMUS THERMOPHILLUS FERMENT [] BEHENYL ALCOHOL [] ACRYLIC ACID/VP CROSSPOLYMER [] TRIACONTANYL PVP [] GLYCERIN [] C12-15 ALKYL BENZOATE [] LINOLEIC ACID [] CHOLESTEROL [] SQUALANE [] SODIUM PCA [] 1,2-HEXANEDIOL [] UREA [] CAPRYLIC/CAPRIC TRIGLYCERIDE [] DIPROPYLENE GLYCOL DIBENZOATE [] TOCOPHERYL ACETATE [] TETRAHEXYLDECYL ASCORBATE [] SODIUM HYALURONATE [] ERGOTHIONEINE [] PPG-15 STEARYL ETHER BENZOATE [] GLYCYRRHETINIC ACID [] TREHALOSE [] POLYQUATERNIUM-51 [] LECITHIN [] HYDROGENATED LECITHIN [] FUMARIC ACID [] PALMITOYL HYDROXYPROPYLTRIMONIUM AMYLOPECTIN/GLYCERIN CROSSPOLYMER [] CAPRYLYL GLYCOL [] CYCLODEXTRIN [] SODIUM HYDROXIDE [] NORDIHYDROGUAIARETIC ACID [] SODIUM CHLORIDE [] ASCORBYL TOCOPHERYL MALEATE [] FRAGRANCE (PARFUM) [] CITRIC ACID [] ETHYLBISIMINOMETHYLGUAIACOL MANGANESE CHLORIDE [] PENTAERYTHRITYL TETRA-DI-T-BUTYL HYDROXYHYDROCINNAMATE [] DISODIUM EDTA [] SODIUM DEHYDROACETATE [] PHENOXYETHANOL [] BUTYLPHENYL METHYLPROPIONAL [] HYDROXYISOHEXYL 3-CYCLOHEXENE CARBOXALDEHYDE [] BENZYL SALICYLATE [] LINALOOL [] BLUE 1 (CI 42090) [] YELLOW 5 (CI 19140) [] CHROMIUM HYDROXIDE GREEN (CI 77289)

WARNINGS

WARNING: KEEP OUT OF EYES. DISCONTINUE USE IF IRRITATION OCCURS.

KEEP OUT OF REACH OF CHILDREN.

PACKAGE LABEL

PRINCIPAL DISPLAY PANEL

ESTEE LAUDER
DAYWEAR
ADVANCED MULTI-PROTECTION
ANTIOXIDANT CREME
SPF 15
FOR NORMAL COMBINATION SKIN
1.7 OZ /50 ML
ESTEE LAUDER DISTR
NEW YORK, NY 10022